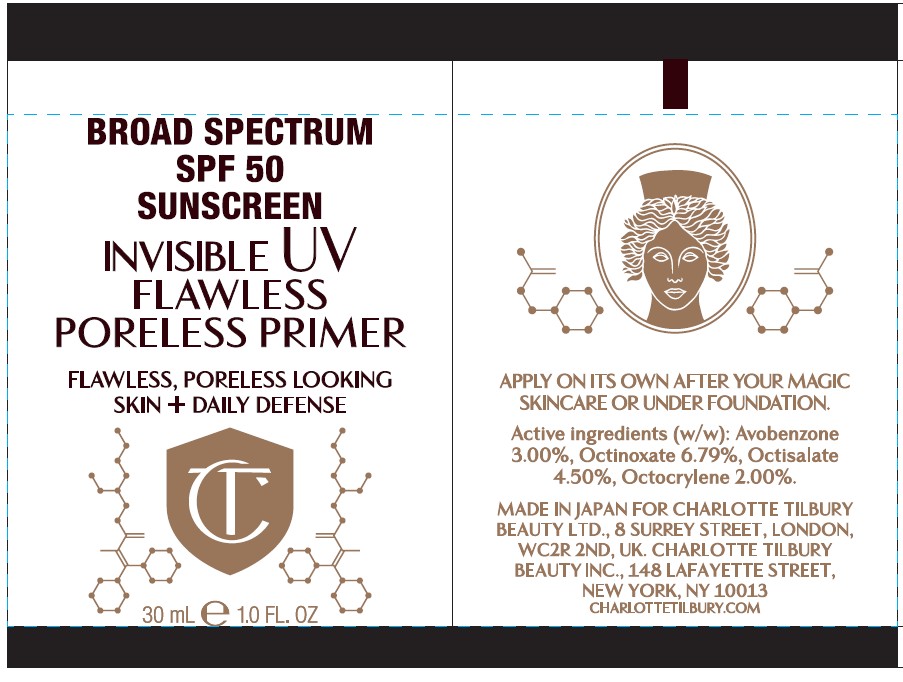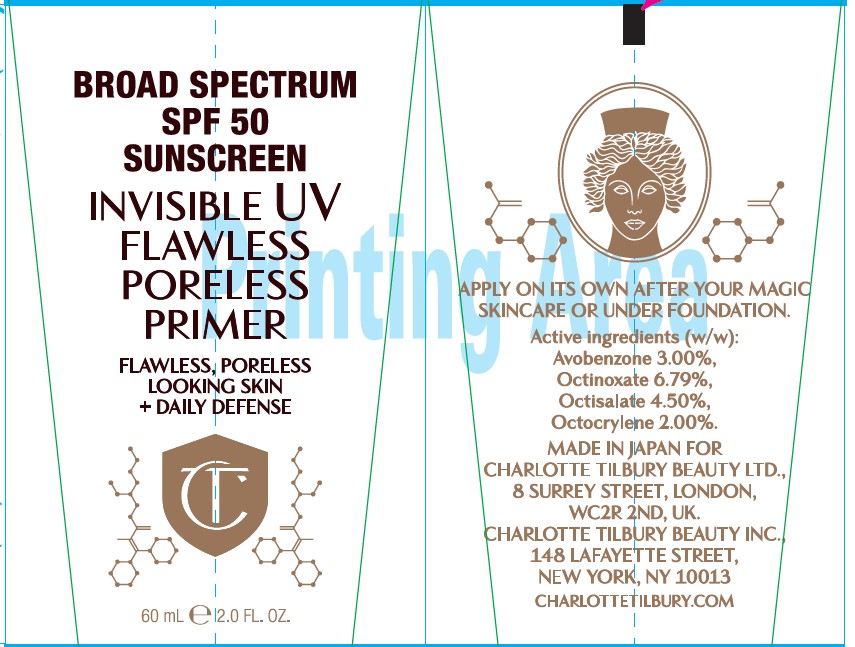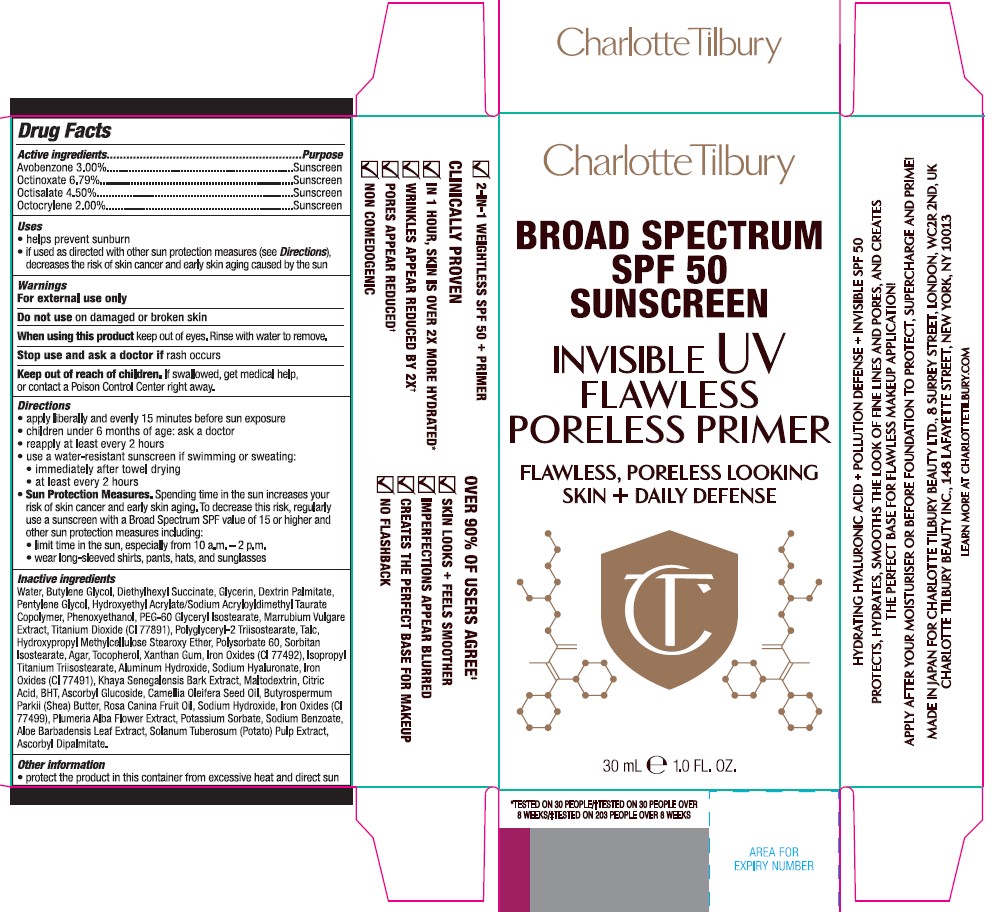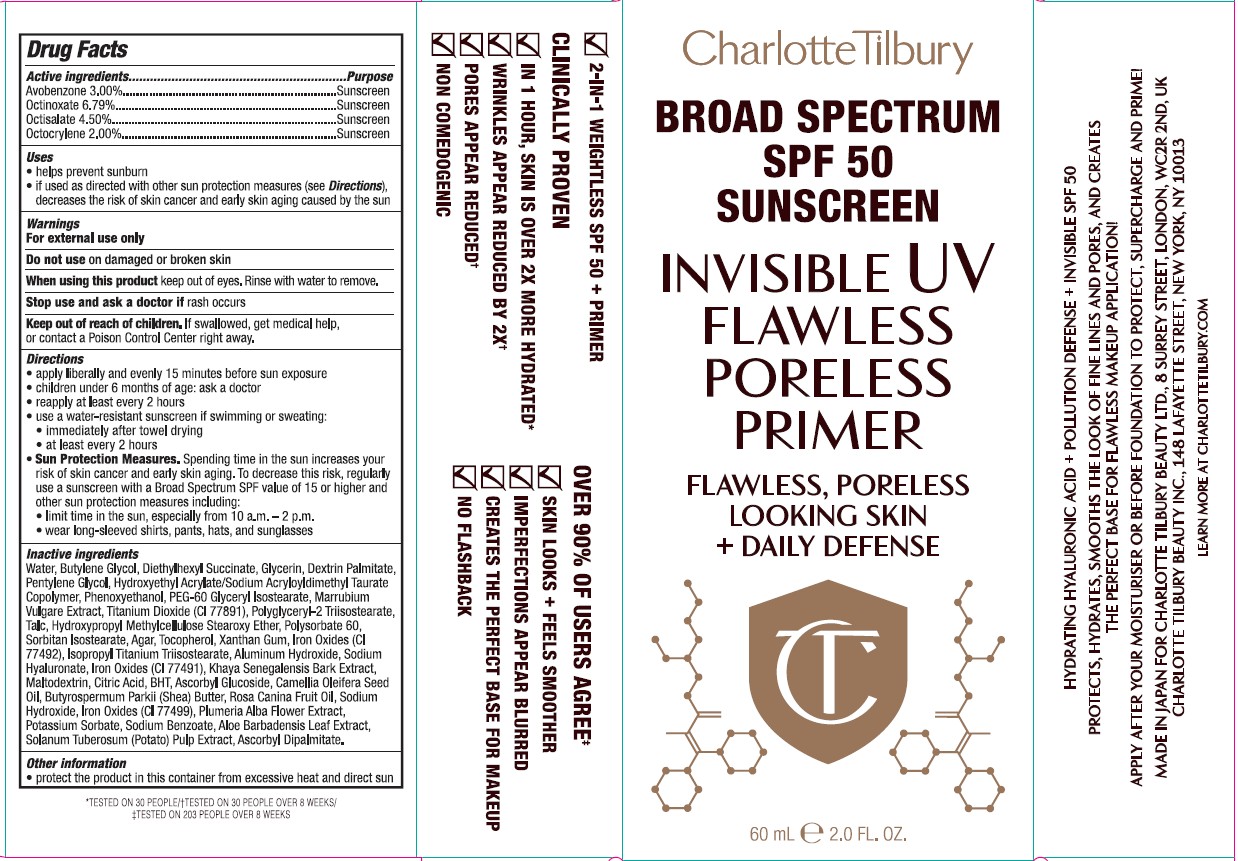 DRUG LABEL: CHARLOTTE TILBURY Broad Spectrum SPF 50 Sunscreen Invisible UV Flawless Poreless Primer
NDC: 70186-701 | Form: CREAM
Manufacturer: Charlotte Tilbury Beauty Ltd.
Category: otc | Type: HUMAN OTC DRUG LABEL
Date: 20251201

ACTIVE INGREDIENTS: AVOBENZONE 0.918 g/30 mL; OCTINOXATE 2.038 g/30 mL; OCTISALATE 1.377 g/30 mL; OCTOCRYLENE 0.612 g/30 mL
INACTIVE INGREDIENTS: POLYSORBATE 60; CITRIC ACID; BUTYROSPERMUM PARKII (SHEA) BUTTER; PLUMERIA ALBA FLOWER; PENTYLENE GLYCOL; PHENOXYETHANOL; POTASSIUM SORBATE; ASCORBYL DIPALMITATE; PEG-60 GLYCERYL ISOSTEARATE; MALTODEXTRIN; CI 77499; ASCORBYL GLUCOSIDE; ROSA CANINA FRUIT OIL; BUTYLENE GLYCOL; HYDROXYETHYL ACRYLATE/SODIUM ACRYLOYLDIMETHYL TAURATE COPOLYMER (100000 MPA.S AT 1.5%); AGAR; CI 77492; ALOE BARBADENSIS LEAF; WATER; ISOPROPYL TITANIUM TRIISOSTEARATE; SODIUM HYALURONATE; CAMELLIA OLEIFERA SEED OIL; GLYCERIN; HOREHOUND; CI 77891; TALC; KHAYA SENEGALENSIS BARK; BHT; POLYGLYCERYL-2 TRIISOSTEARATE; CI 77491; DEXTRIN PALMITATE (CORN; 20000 MW); SORBITAN ISOSTEARATE; XANTHAN GUM; ALUMINUM HYDROXIDE; SODIUM HYDROXIDE; POTATO PULP; TOCOPHEROL; DIETHYLHEXYL SUCCINATE; HYDROXYPROPYL METHYLCELLULOSE; SODIUM BENZOATE

CHARLOTTE TILBURY INVISIBLE UV FLAWLESS PORELESS PRIMER

Active ingredients...............Purpose

Avobenzone 3.00%............Sunscreen

Octinoxate 6.79%...............Sunscreen

Octisalate 4.50%................Sunscreen

Octocrylene 2.00%.............Sunscreen

Active ingredients...............Purpose

Avobenzone 3.00%............Sunscreen

Octinoxate 6.79%...............Sunscreen

Octisalate 4.50%................Sunscreen

Octocrylene 2.00%.............Sunscreen

Uses

- helps prevent sunburn
- if used as directed with other sun protection measures (see Directions), decreases the risk of skin cancer and early skin aging caused by the sun

WARNINGS

For external use only

Do not use on damaged or broken skin

When using this product keep out of eyes. Rinse with water to remove.

Stop use and ask a doctor if rash occurs

Keep out of reach of children. If swallowed, get medical help, or contact a Poison Control Center right away.

Directions

- apply liberally and evenly 15 minutes before sun exposure
- children under 6 months of age: ask a doctor
- reapply at least every 2 hours
- use a water-resistant sunscreen if swimming or sweating:
- immediately after towel drying
- at least every 2 hours
- Sun Protection Measures. Spending time in the sun increases your risk of skin cancer and early skin aging. To decrease this risk, regularly use a sunscreen with a Broad Spectrum SPF value of 15 or higher and other sun protection measures including:
- limit time in the sun, especially from 10 a.m.-2 p.m.
- wear long-sleeved shirts, pants, hats, and sunglasses

Inactive ingredients

Water, Butylene Glycol, Diethylhexyl Succinate, Glycerin, Dextrin Palmitate, Pentylene Glycol, Hydroxyethyl Acrylate/Sodium Acryloyldimethyl Taurate Copolymer, Phenoxyethanol, PEG-60 Glyceryl Isostearate, Marrubium Vulgare Extract, Titanium Dioxide (CI 77891), Polyglyceryl-2 Triisostearate, Talc, Hydroxypropyl Methylcellulose Stearoxy Ether, Polysorbate 60, Sorbitan Isostearate, Agar, Tocopherol, Xanthan Gum, Iron Oxides (CI 77492), Isopropyl Titanium Triisostearate, Aluminum Hydroxide, Sodium Hyaluronate, Iron Oxides (CI 77491), Khaya Senegalensis Bark Extract, Maltodextrin, Citric Acid, BHT, Ascorbyl Glucoside, Camellia Oleifera Seed Oil, Butyrospermum Parkii (Shea) Butter, Rosa Canina Fruit Oil, Sodium Hydroxide, Iron Oxides (CI 77499), Plumeria Alba Flower Extract, Potassium Sorbate, Sodium Benzoate, Aloe Barbadensis Leaf Extract, Solanum Tuberosum (Potato) Pulp Extract, Ascorbyl Dipalmitate.

Other information

- protect the product in this container from excessive heat and direct sun

Principal Display Panel - 30 mL e 1.0 fl. oz

Inner label - 30 mL

Outer label - 30 mL

Principal Display Panel - 60 mL e 2.0 fl. oz

Inner label - 60 mL

Outer label - 60 mL